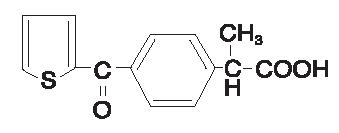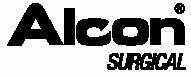 DRUG LABEL: Unknown
Manufacturer: Alcon Laboratories, Inc.
Category: prescription | Type: Human Prescription Drug Label
Date: 20060223

Profenal® 1%
(Suprofen)
Sterile Ophthalmic Solution

DESCRIPTION

PROFENAL® (suprofen) 1% ophthalmic solution is a topical nonsteroidal anti-inflammatory product for ophthalmic use. Suprofen chemically is α -methyl-4-(2-thienylcarbonyl)benzeneacetic acid, with an empirical formula of C14H12O3S, and a molecular weight of 260.3. The chemical structure of suprofen is:

PROFENAL Sterile Ophthalmic Solution contains suprofen 1.0% (10 mg/mL), thimerosal 0.005% (0.05 mg/mL), caffeine 2% (20 mg/mL), edetate disodium, dibasic sodium phosphate, monobasic sodium phosphate, sodium chloride, sodium hydroxide and/or hydrochloric acid (to adjust pH to 7.4) and purified water.

DM-00

CLINICAL PHARMACOLOGY

Suprofen is one of a series of phenylalkanoic acids that have shown analgesic, antipyretic, and anti-inflammatory activity in animal inflammatory diseases. Its mechanism of action is believed to be through inhibition of the cyclooxygenase enzyme that is essential in the biosynthesis of prostaglandins.

Prostaglandins have been shown in many animal models to be mediators of certain kinds of intraocular inflammation. In studies performed on animal eyes, prostaglandins have been shown to produce disruption of the blood-aqueous humor barrier, vasodilatation, increased vascular permeability, leukocytosis, and increased intraocular pressure.

Prostaglandins appear to play a role in the miotic response produced during ocular surgery by constricting the iris sphincter independently of cholinergic mechanisms. In clinical studies, PROFENAL has been shown to inhibit the miosis induced during the course of cataract surgery. PROFENAL could possibly interfere with the miotic effect of intraoperatively administered acetylcholine chloride.

Results from clinical studies indicate that PROFENAL Ophthalmic Solution has no significant effect on intraocular pressure.

There are no data available on the systemic absorption of ocularly applied suprofen. The oral dose of suprofen is 200 mg every four to six hours. If PROFENAL 1% Ophthalmic Solution is applied as two drops (1 mg suprofen) to one eye five times on the day prior to surgery and three times on the day of surgery, the total applied dose over the two days would be about 25 times less than a single 200 mg oral dose.

INDICATIONS AND USAGE

PROFENAL Ophthalmic Solution is indicated for inhibition of intraoperative miosis.

CONTRAINDICATIONS

PROFENAL is contraindicated in epithelial herpes simplex keratitis (dendritic keratitis) and in individuals hypersensitive to any component of the medication.

WARNINGS

The potential exists for cross sensitivity to acetylsalicylic acid and other nonsteroidal anti-inflammatory drugs. Therefore, caution should be used when treating individuals who have previously exhibited sensitivities to these drugs.

With nonsteroidal anti-inflammatory drugs, the potential exists for increased bleeding time due to interference with thrombocyte aggregation. There have been reports that ocularly applied nonsteroidal anti-inflammatory drugs may cause increased bleeding tendency of ocular tissues in conjunction with ocular surgery.

PRECAUTIONS

General

Use of oral suprofen has been associated with a syndrome of acute flank pain and generally reversible renal insufficiency, which may present as acute uric acid nephropathy. This syndrome occurs in approximately 1 in 3500 patients and has been reported with as few as one to two doses of a 200 mg capsule. If PROFENAL 1% Ophthalmic Solution is applied as two drops (1 mg suprofen) to one eye five times on the day prior to surgery and three times on the day of surgery, the total applied dose over the two days would be about 25 times less than a single 200 mg oral dose. Do not touch dropper tip to any surface, as this may contaminate the solution.

Ocular

Patients with histories of herpes simplex keratitis should be monitored closely. PROFENAL is contraindicated in patients with active herpes simplex keratitis.

The possibility of increased ocular bleeding during surgery associated with nonsteroidal anti-inflammatory drugs should be considered.

Carcinogenesis, Mutagenesis, Impairment of Fertility

In an 18-month study in mice, an increased incidence of benign hepatomas occurred in females at a dose of 40 mg/kg/day. Male mice, treated at doses of 2, 5, 10 and 40 mg/kg/day, also had an increased incidence of hepatomas when compared to control animals. No evidence of carcinogenicity was found in long term studies in doses as high as 40 mg/kg/day in the rat and mouse. Based on a battery of mutagenicity tests (Ames, micronucleus, and dominant lethal), suprofen does not appear to have mutagenic potential. Reproductive studies in rats at a dose of up to 40 mg/kg/day revealed no impairment of fertility and only slight reductions of fertility at doses of 80 mg/kg/day. However, testicular atrophy/hypoplasia was observed in a six-month dog study (at 80 mg/kg/day) and a 12-month rat study (at 40 mg/kg/day).

Pregnancy Category C

Reproductive studies have been performed in rabbits at doses up to 200 mg/kg/day and in rats at doses up to 80 mg/kg/day. In rats, doses of 40 mg/kg/day and above, and in rabbits, doses of 80 mg/kg/day and above, resulted in an increased incidence of fetal resorption associated with maternal toxicity. There was an increase in stillbirths and a decrease in postnatal survival in pregnant rats treated with suprofen at 2.5 mg/kg/day and above. An increased incidence of delayed parturition occurred in rats. As there are no adequate and well-controlled studies in pregnant women, this drug should be used during pregnancy only if the potential benefit justifies the potential risk to the fetus. Because of the known effect of nonsteroidal anti-inflammatory drugs on the fetal cardiovascular system (closure of ductus arteriosus), use during late pregnancy should be avoided.

Nursing Mothers

Suprofen is excreted in human milk after a single oral dose. Based on measurements of plasma and milk levels in women taking oral suprofen, the milk concentration is about 1% of the plasma level. Because systemic absorption may occur from topical ocular administration, a decision should be considered to discontinue nursing while receiving PROFENAL®, since the safety of suprofen in human neonates has not been established.

Pediatric Use

Safety and effectiveness in pediatric patients have not been established.

Drug Interactions

Clinical studies with acetylcholine chloride revealed no interference, and there is no known pharmacological basis for such an interaction. However, with other topical nonsteroidal anti-inflammatory products, there have been reports that acetylcholine chloride and carbachol have been ineffective when used in patients treated with these agents.

Interaction of PROFENAL with other topical ophthalmic medications has not been fully investigated.

ADVERSE REACTIONS

Ocular

The most frequent adverse reactions reported are burning and stinging of short duration. Instances of discomfort, itching and redness have been reported. Other reactions occurring in less than 0.5% of patients include allergy, iritis, pain, chemosis, photophobia, irritation, and punctate epithelial staining.

Systemic

Systemic reactions related to therapy were not reported in the clinical studies. It is known that some systemic absorption does occur with ocularly applied drugs, and that nonsteroidal anti-inflammatory drugs have been shown to increase bleeding time by interference with thrombocyte aggregation. It is recommended that PROFENAL be used with caution in patients with bleeding tendencies and those taking anticoagulants.

OVERDOSAGE

Overdosage will not ordinarily cause acute problems. If accidentally ingested, drink fluids to dilute.

DOSAGE AND ADMINISTRATION

On the day of surgery, instill two drops into the conjunctival sac at three, two and one hour prior to surgery. Two drops may be instilled into the conjunctival sac every four hours, while awake, the day preceding surgery.

HOW SUPPLIED

Sterile ophthalmic solution, 2.5 mL in plastic DROP-TAINER® dispensers.

2.5 mL NDC 0065-0348-25

STORAGE: Store at room temperature.

Rx Only

U.S. Patents Nos. 4,035,376; 4,559,343

Alcon Laboratories, Inc.
Fort Worth, Texas 76134 USA

Printed in USA

343005-0798 Revised: July 1998